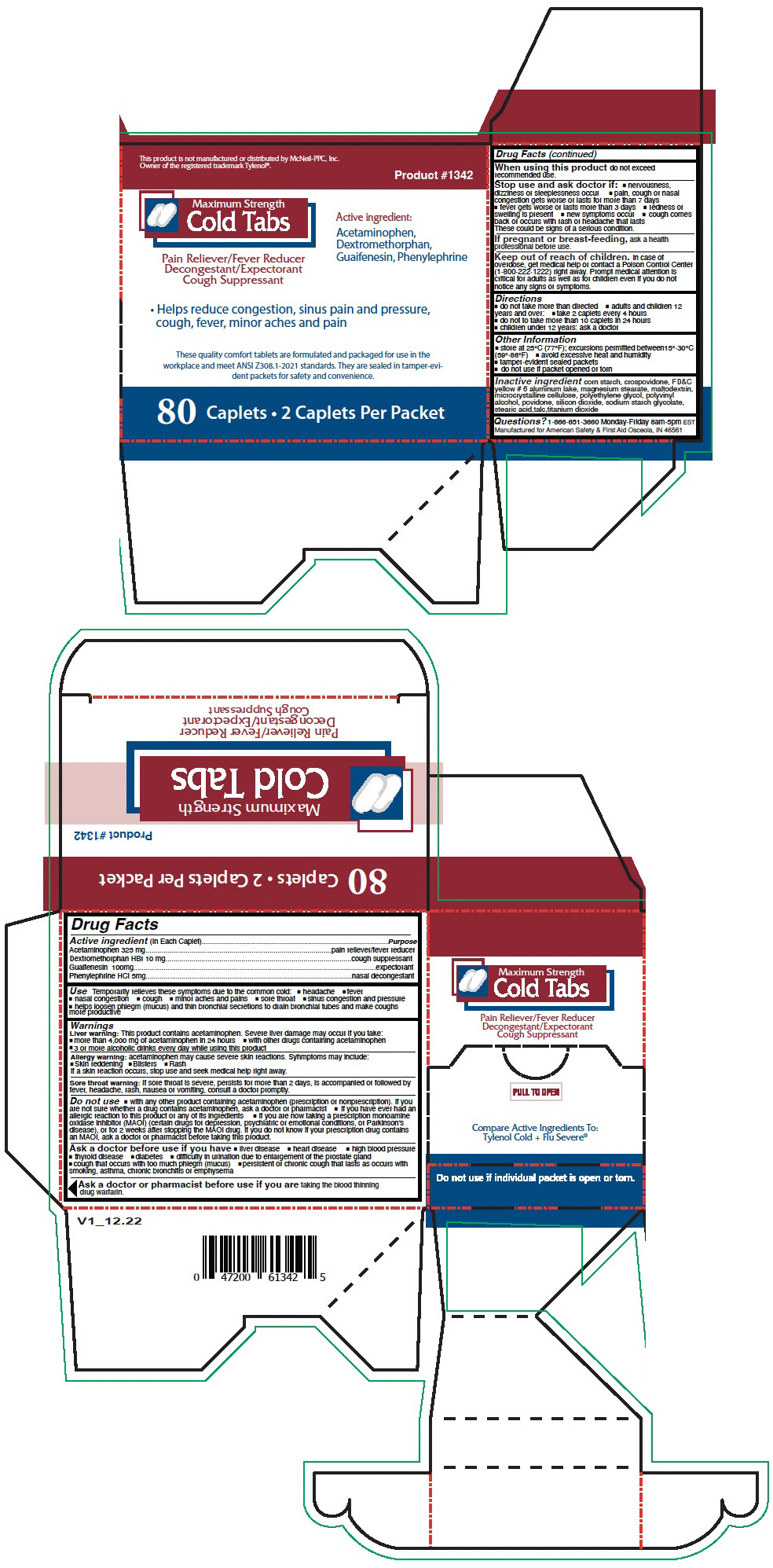 DRUG LABEL: Maximum Strength Cold Tabs
NDC: 73598-1342 | Form: CAPSULE, COATED
Manufacturer: JHK DBA American Safety & First Aid
Category: otc | Type: HUMAN OTC DRUG LABEL
Date: 20240715

ACTIVE INGREDIENTS: ACETAMINOPHEN 325 mg/1 1; DEXTROMETHORPHAN HYDROBROMIDE 10 mg/1 1; GUAIFENESIN 100 mg/1 1; PHENYLEPHRINE HYDROCHLORIDE 5 mg/1 1
INACTIVE INGREDIENTS: STARCH, CORN; CROSPOVIDONE, UNSPECIFIED; FD&C YELLOW NO. 6 ALUMINUM LAKE; MAGNESIUM STEARATE; MALTODEXTRIN; MICROCRYSTALLINE CELLULOSE; POLYETHYLENE GLYCOL, UNSPECIFIED; POLYVINYL ALCOHOL, UNSPECIFIED; POVIDONE, UNSPECIFIED; SILICON DIOXIDE; SODIUM STARCH GLYCOLATE TYPE A; STEARIC ACID; TALC; TITANIUM DIOXIDE

Maximum Strength Cold Tabs

Drug Facts

ACTIVE INGREDIENT

Active ingredient (In Each Caplet) | Purpose
Acetaminophen 325 mg | pain reliever/fever reducer
Dextromethorphan HBr 10 mg | cough suppressant
Guaifenesin 100mg | expectorant
Phenylephrine HCl 5mg | nasal decongestant

Use

Temporarily relieves these symptoms due to the common cold:

- headache
- fever
- nasal congestion
- cough
- minor aches and pains
- sore throat
- sinus congestion and pressure
- helps loosen phlegm (mucus) and thin bronchial secretions to drain bronchial tubes and make coughs more productive

Warnings

Liver warning

This product contains acetaminophen. Severe liver damage may occur if you take:

- more than 4,000 mg of acetaminophen in 24 hours
- with other drugs containing acetaminophen
- 3 or more alcoholic drinks every day while using this product

Allergy warning: acetaminophen may cause severe skin reactions. Syhmptoms may include:

- Skin reddening
- Blisters
- Rash

If a skin reaction occurs, stop use and seek medical help right away.

Sore throat warning

If sore throat is severe, persists for more than 2 days, is accompanied or followed by fever, headache, rash, nausea or vomiting, consult a doctor promptly.

Do not use

- with any other product containing acetaminophen (prescription or nonprescription). If you are not sure whether a drug contains acetaminophen, ask a doctor or pharmacist
- if you have ever had an allergic reaction to this product or any of its ingredients
- if you are now taking a prescription monoamine oxidase inhibitor (MAOI) (certain drugs for depression, psychiatric or emotional conditions, or Parkinson's disease), or for 2 weeks after stopping the MAOI drug. If you do not know if your prescription drug contains an MAOI, ask a doctor or pharmacist before taking this product.

Ask a doctor before use if you have

- liver disease
- heart disease
- high blood pressure
- thyroid disease
- diabetes
- difficulty in urination due to enlargement of the prostate gland
- cough that occurs with too much phlegm (mucus)
- persistent or chronic cough that lasts as occurs with smoking, asthma, chronic bronchitis or emphysema

Ask a doctor or pharmacist before use if you are taking the blood thinning drug warfarin.

When using this product do not exceed recommended use.

Stop use and ask doctor if:

- nervousness, dizziness or sleeplessness occur
- pain, cough or nasal congestion gets worse or lasts for more than 7 days
- fever gets worse or lasts more than 3 days
- redness or swelling is present
- new symptoms occur
- cough comes back or occurs with rash or headache that lasts

These could be signs of a serious condition.

PREGNANCY OR BREAST FEEDING

If pregnant or breast-feeding, ask a health professional before use.

Keep out of reach of children. In case of overdose, get medical help or contact a Poison Control Center (1-800-222-1222) right away. Prompt medical attention is critical for adults as well as for children even if you do not notice any signs or symptoms.

Directions

- do not take more than directed
- adults and children 12 years and over:
  - take 2 caplets every 4 hours
  - do not to take more than 10 caplets in 24 hours
- children under 12 years: ask a doctor

Other Information

- store at 25°C (77°F); excursions permitted between15°-30°C (59°-86°F)
- avoid excessive heat and humidity
- tamper-evident sealed packets
- do not use if packet opened or torn

Inactive ingredient

corn starch, crospovidone, FD&C yellow # 6 aluminum lake, magnesium stearate, maltodextrin, microcrystalline cellulose, polyethylene glycol, polyvinyl alcohol, povidone, silicon dioxide, sodium starch glycolate, stearic acid,talc,titanium dioxide

Questions?

1-866-651-3660 Monday-Friday 8am-5pm EST

PRINCIPAL DISPLAY PANEL - 80 Caplet Packet Box

This product is not manufactured or distributed by McNeil-PPC, Inc.
Owner of the registered trademark Tylenol®.

Product #1342

Maximum Strength
Cold Tabs

Pain Reliever/Fever Reducer
Decongestant/Expectorant
Cough Suppressant

Active ingredient:
Acetaminophen,
Dextromethorphan,
Guaifenesin, Phenylephrine

- Helps reduce congestion, sinus pain and pressure,
  cough, fever, minor aches and pain

These quality comfort tablets are formulated and packaged for use in the
workplace and meet ANSI Z308.1-2021 standards. They are sealed in tamper-evi-
dent packets for safety and convenience.

80 Caplets • 2 Caplets Per Packet